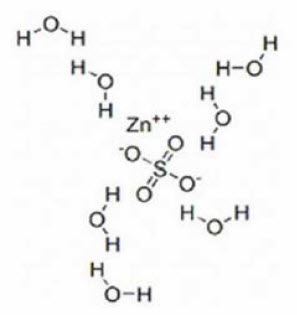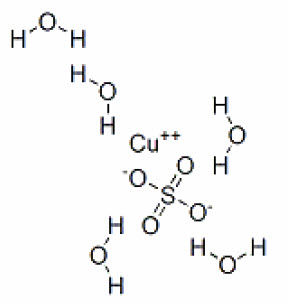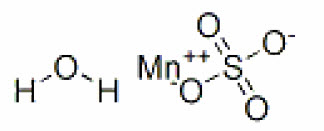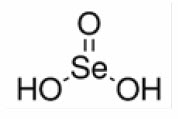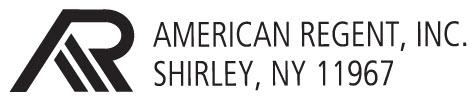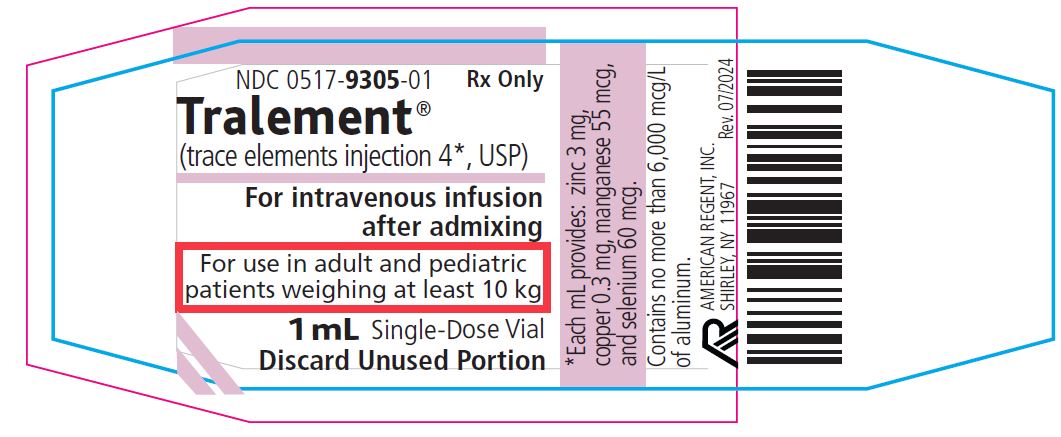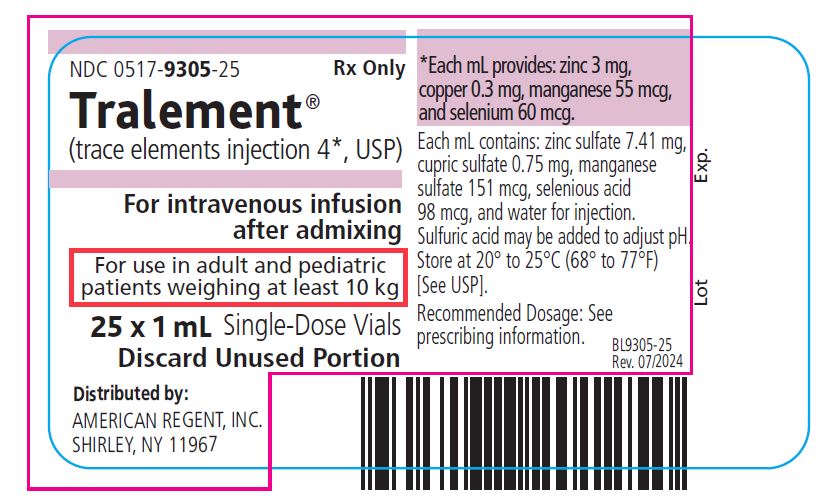 DRUG LABEL: Tralement
NDC: 0517-9305 | Form: INJECTION, SOLUTION
Manufacturer: American Regent, Inc.
Category: prescription | Type: HUMAN PRESCRIPTION DRUG LABEL
Date: 20240701

ACTIVE INGREDIENTS: ZINC SULFATE 3 mg/1 mL; CUPRIC SULFATE 0.3 mg/1 mL; MANGANESE SULFATE 55 ug/1 mL; SELENIOUS ACID 60 ug/1 mL
INACTIVE INGREDIENTS: WATER

HIGHLIGHTS OF PRESCRIBING INFORMATION

These highlights do not include all the information needed to use TRALEMENT® safely and effectively. See full prescribing information for TRALEMENT® .
TRALEMENT® (trace elements injection 4*) for intravenous use
Initial U.S. Approval: 2020

1 INDICATIONS AND USAGE

Tralement is a combination of trace elements (zinc sulfate, cupric sulfate, manganese sulfate and selenious acid) indicated in adult and pediatric patients weighing at least 10 kg as a source of zinc, copper, manganese, and selenium for parenteral nutrition when oral or enteral nutrition is not possible, insufficient, or contraindicated. (1)

2 DOSAGE AND ADMINISTRATION

- Single-dose vial amd multiple-dose vial. Not for direct intravenous infusion. (2.1)
- See full prescribing information for information on preparation, administration and general dosing considerations. (2.1, 2.2, 2.3, 2.4)
  Recommended Dosage
- Each mL of Tralement provides zinc 3 mg, copper 0.3 mg, manganese 55 mcg, and selenium 60 mcg. (2.5)
- Adults and Pediatric Patients Weighing at Least 50 kg: The recommended dosage of Tralement is 1 mL per day added to parenteral nutrition.
  Tralement is not recommended for patients who may require a lower dosage of one or more of the individual trace elements. (2.5)
- Pediatric Patients Weighing 10 kg to 49 kg: The recommended dosage of Tralement based on body weight is 0.2 mL to 0.8 mL per day added to
  parenteral nutrition. Tralement does not provide the recommended daily dosage of zinc (in heavier patients in some weight bands), copper or selenium. Additional supplementation using single trace element products may be needed for these patients. For complete dosing information see table in the full prescribing information. (2.4, 2.5)
- Monitor trace element concentrations in blood during long-term administration of parenteral nutrition. (2.5)

3 DOSAGE FORMS AND STRENGTHS

Injection: (3)

- 1 mL in a single-dose vial and 10 mL in a multiple-dose vial. Each mL contains zinc 3 mg, copper 0.3 mg, manganese 55 mcg, and selenium 60 mcg.

4 CONTRAINDICATIONS

Hypersensitivity to zinc or copper (4,5.7)

5 WARNINGS AND PRECAUTIONS

- Pulmonary Embolism due to Pulmonary Vascular Precipitates: If signs of pulmonary distress occur, stop the infusion and initiate a medical evaluation. (5.1)
- Vein Damage and Thrombosis: Solutions with osmolarity of 900 mOsmol/L or more must be infused through a central catheter. (2.1, 5.2)
- Neurologic Toxicity with Manganese: Monitor for clinical signs and symptoms of neurotoxicity, whole blood manganese concentrations and liver function tests in patients receiving long-term Tralement. Discontinue Tralement and consider brain magnetic resonance imaging (MRI) if toxicity suspected. (5.3)
- Hepatic Accumulation of Copper and Manganese: Assess for development of hepatic or biliary dysfunction. Monitor concentrations of copper and manganese in patients with cholestasis, biliary dysfunction or cirrhosis receiving Tralement long-term. (5.4)
- Aluminum Toxicity: Increased risk in patients with renal impairment, including preterm infants. (5.5, 8.4)
- Monitoring and Laboratory Tests: Monitor blood zinc, copper, manganese, and selenium concentrations, fluid and electrolyte status, serum osmolarity, blood glucose, liver and kidney function, blood count and coagulation parameters. (5.6, 2.4)
- Hypersensitivity Reactions with Zinc and Copper: If reactions occur, discontinue Tralement and initiate appropriate medical treatment. (5.7)

To report SUSPECTED ADVERSE REACTIONS, contact American Regent, Inc. at 1-800-734-9236 or FDA at 1-800-FDA-1088 or www.fda.gov/medwatch.

6 ADVERSE REACTIONS

No adverse reactions related to zinc, copper, selenium, or manganese have been reported in patients receiving intravenously administered parenteral solutions containing these trace elements within the recommended dosage range. (6)

To report SUSPECTED ADVERSE REACTIONS, contact Actavis at 1-800-432-8534 or FDA at 1-800-FDA-1088, or www.fda.gov/medwatch.

8 USE IN SPECIFIC POPULATIONS

Pediatric Patients Weighing Less than 10 kg: Tralement is not approved for use in this subpopulation because the product does not provide an adequate dosage of zinc, copper, or selenium and exceeds the recommended dosage of manganese. (8.4)

FULL PRESCRIBING INFORMATION

1 INDICATIONS AND USAGE

Tralement® is indicated in adult and pediatric patients weighing at least 10 kg as a source of zinc, copper, manganese, and selenium for parenteral nutrition when oral or enteral nutrition is not possible, insufficient, or contraindicated.

2 DOSAGE AND ADMINISTRATION

2.1 Important Administration Information

Tralement is supplied as a single-dose vial and multiple-dose vial for admixture use only. It is not for direct intravenous infusion. Prior to administration, Tralement must be transferred to a separate parenteral nutrition container and used as an admixture in parenteral nutrition solution.

The final parenteral nutrition solution is for intravenous infusion into a central or peripheral vein. The choice of a central or peripheral venous route should depend on the osmolarity of the final infusate. Solutions with osmolarity of 900 mOsmol/L or greater must be infused through a central catheter [see Warnings and Precautions (5.2)].

2.2 Preparation and Administration Instructions

- Tralement is not for direct intravenous infusion. Prior to administration, Tralement must be prepared and used as an admixture in parenteral nutrition solution.
- Add Tralement to the parenteral nutrition solution in a suitable work area such as a laminar flow hood (or an equivalent clean air compounding area). The key factor in the preparation is careful aseptic technique to avoid inadvertent touch contamination during mixing of solutions and addition of other nutrients.
- Inspect the parenteral nutrition solution containing Tralement for particulate matter before admixing, after admixing, and prior to administration.

2.3 Preparation Instructions for Admixing Using a Parenteral Nutrition Container

- Inspect Tralement single-dose vial and multiple-dose vial for particulate matter.
- Transfer Tralement to the parenteral nutrition container after the admixture of amino acids, dextrose, lipid emulsion (if added), and electrolytes solutions is prepared.
- Because additives may be incompatible, evaluate all additions to the parenteral nutrition container for compatibility and stability of the resulting preparation. Consult with pharmacist, if available. For introducing additives to the parenteral nutrition container, use aseptic technique.
- An interaction may occur between cupric ion and ascorbic acid; therefore, multivitamin additives should be added to the admixed parenteral nutrition solution shortly before infusion.
- Inspect the final parenteral nutrition solution containing Tralement to ensure that:
  o Precipitates have not formed during mixing or addition on additives.
  o The emulsion has not separated, if lipid emulsion has been added. Separation of the emulsion can be visibly identified by a yellowish streaking or the accumulation of yellowish droplets in the admixed emulsion.
  o Discard if any precipitates are observed.

Stability and Storage

- Single-dose vial. Discard unused portion.
- Multiple-dose vial: May puncture up to 20 times. Discard any unused portion after 28 days.
- Use parenteral nutrition solutions containing Tralement promptly after mixing. Any storage of the admixture should be under refrigeration from 2ºC to 8ºC (36ºF to 46ºF) and limited to a period of no longer than 9 days. After removal from refrigeration, use promptly and complete the infusion within 24 hours. Discard any remaining admixture.
- Protect the parenteral nutrition solution from light.

2.4 Overview of Dosing

- Prior to administration of parenteral nutrition solution containing Tralement, correct severe fluid, electrolyte, and acid-base disorders.
- The dosage of the final parenteral nutrition solution containing Tralement must be based on the concentrations of all components in the solution, the patient’s clinical condition, nutritional requirements, and the contribution of oral or enteral intake.
- For pediatric patients weighing 10 to 49 kg, Tralement does not provide the recommended daily dosage of zinc (in heavier patients in some weight bands), copper or selenium. Additional supplementation using single trace element products may be needed for these patients [see Dosage and Administration (2.5)].
- Monitor fluid and electrolyte status during treatment use of Tralement and adjust the parenteral nutrition solution as needed

2.5 Recommended Dosage and Monitoring in Adult and Pediatric Patients

Tralement is a fixed-combination product. Each mL of Tralement provides zinc 3 mg, copper 0.3 mg, manganese 55 mcg, and selenium 60 mcg.

Tralement is recommended only for patients who require supplementation with all four of the individual trace elements (i.e., zinc, copper, manganese and selenium).

Adults and Pediatric Patients Weighing at least 50 kg:
The recommended dosage of Tralement is 1 mL per day added to parenteral nutrition (zinc 3 mg/copper 0.3 mg/manganese 55 mcg/selenium 60 mcg). Tralement is not recommended for those patients who may require a lower dosage of one or more of the individual trace elements.

Pediatric Patients Weighing 10 kg to 49 kg:
The recommended dosage of Tralement by volume to be added to parenteral nutrition is based on body weight and ranges from 0.2 mL to 0.8 mL per day as shown in Table 1.

Body Weight | Recommended Weight-Based Dosage of Tralement in Volume | Amount of Trace Element Provided by the Corresponding Tralement Volume
Body Weight | Recommended Weight-Based Dosage of Tralement in Volume | Zinc | Copper | Manganese | Selenium
10 kg to 19 kg | 0.2 mL | 600 mcg | 60 mcg | 11 mcg | 12 mcg
20 kg to 29 kg | 0.4 mL | 1,200 mcg | 120 mcg | 22 mcg | 24 mcg
30 kg to 39 kg | 0.6 mL | 1,800 mcg | 180 mcg | 33 mcg | 36 mcg
40 kg to 49 kg | 0.8 mL | 2,400 mcg | 240 mcg | 44 mcg | 48 mcg

Use Additional Supplementation with Tralement
For pediatric patients weighing 10 kg to 49 kg, additional zinc (in heavier patients in some weight bands), copper and selenium may be needed to meet the recommended daily dosage of these trace elements, shown below. To determine the additional amount of supplementation that is needed, compare the calculated daily recommended dosage based on the body weight of the patient to the amount of each trace element provided by Tralement (Table 1) and other oral or enteral nutrition sources.

- Zinc: 50 mcg/kg/day (up to 3,000 mcg/day)
- Copper: 20 mcg/kg/day (up to 300 mcg/day)
- Selenium: 2 mcg/kg/day (up to 60 mcg/day)

Do not supplement Tralement with additional manganese. Accumulation of manganese in the brain can occur with long-term administration with higher than the recommended dosage of 1 mcg/kg/day (up to 55 mcg/day) [see Warnings and Precautions (].
Monitoring

- Monitor serum zinc, copper, and selenium concentrations and manganese whole blood concentrations during long-term administration of parenteral nutrition.
- Trace elements concentrations may vary depending on the assay used and the laboratory reference range. The collection, processing, and storage of the blood samples should be performed according to the laboratory’s sample requirements for analysis.
  o Zinc: In serum, the reported concentration range in healthy adults is 60 to 140 mcg/dL. Zinc concentrations in hemolyzed samples may be falsely elevated due to release of zinc from erythrocytes.
  o Copper: In serum, the reported concentration range in healthy adults is 70 to 175 mcg/dL; consider obtaining concentrations of ceruloplasmin along with serum copper.
  o Manganese: In whole blood, the reported concentration range in healthy adults is 4 to 16 mcg/L.
  o Selenium: In serum, the reported concentration range in healthy adults is 7 to 19 mcg/dL.

3 DOSAGE FORMS AND STRENGTHS

Injection: Clear, colorless to slightly blue solution in a 1 mL single-dose vial and 10 mL multiple-dose vial.

Each mL contains zinc 3 mg, copper 0.3 mg, manganese 55 mcg, and selenium 60 mcg.

4 CONTRAINDICATIONS

Tralement is contraindicated in patients with hypersensitivity to zinc or copper [see Warnings and Precautions (5.7)].

5 WARNINGS AND PRECAUTIONS

5.1 Pulmonary Embolism due to Pulmonary Vascular Precipitates

Pulmonary vascular precipitates causing pulmonary vascular emboli and pulmonary distress have been reported in patients receiving parenteral nutrition. The cause of precipitate formation has not been determined in all cases; however, in some fatal cases, pulmonary emboli occurred as a result of calcium phosphate precipitates. Precipitation has occurred following passage through an in-line filter; in vivo precipitate formation may also have occurred. If signs of pulmonary distress occur, stop the parenteral nutrition infusion and initiate a medical evaluation. In addition to inspection of the solution [see Dosage and Administration (2.2, 2.3)], the infusion set, and catheter should also periodically be checked for precipitates.

5.2 Vein Damage and Thrombosis

Tralement must be prepared and used as an admixture in parenteral nutrition solution. It is not for direct intravenous infusion. In addition, consider the osmolarity of the final parenteral nutrition solution in determining peripheral versus central administration. Solution with an osmolarity of 900 mOsmol/L or
greater must be infused through a central catheter [see Dosage and Administration (2.1)]. The infusion of hypertonic nutrient solution into a peripheral vein may result in vein irritation, vein damage, and/or thrombosis. The primary complication of peripheral access is venous thrombophlebitis, which manifests
as pain, erythema, tenderness or a palpable cord. Remove the catheter as soon as possible, if thrombophlebitis develops.

5.3 Neurologic Toxicity with Manganese

Manganese accumulation in the basal ganglia has been reported in adult and pediatric patients on long-term parenteral nutrition receiving manganese at higher than recommended dosages and in association with cholestatic liver disease. Some adult patients with brain MRI findings reportedly experienced neuropsychiatric symptoms, including changes in mood or memory, seizures and/or parkinsonian-like tremors, dysarthria, mask-face, and halting gait. Some pediatric patients experienced dystonic movements or seizures. Brain MRI findings and clinical symptoms have also been observed in patients who received manganese at or below the recommended dosage and with normal blood manganese concentrations. Regression of symptoms and MRI findings have occurred over weeks to months following discontinuation of manganese in most patients but have not always completely resolved.

Monitor patients receiving long-term parenteral nutrition solutions containing Tralement for neurologic signs and symptoms and routinely monitor whole blood manganese concentrations and liver function tests. In case of suspected manganese toxicity or new neuro-psychiatric manifestations, temporarily discontinue Tralement, check manganese whole blood concentrations, and consider brain MRI evaluation.

Monitor patients receiving Tralement for cholestasis or other biliary liver disease. Consider individual trace element products as an alternative to Tralement in patients with hepatic and/or biliary dysfunction [see Warnings and Precautions (5.4)].

5.4 Hepatic Accumulation of Copper and Manganese

Copper is primarily eliminated in the bile and excretion is decreased in patients with cholestasis and/or cirrhosis. Hepatic accumulation of copper and manganese have been reported in autopsies of patients receiving long-term parenteral nutrition containing copper and manganese at dosages higher
than recommended.

Patients receiving parenteral nutrition with cholestasis and/or cirrhosis are at increased risk of manganese brain deposition and neurotoxicity [see Warnings and Precautions (5.3)].

Administration of copper to patients with cholestasis, and/or cirrhosis may cause hepatic accumulation of copper. Administration of copper to patients with Wilson disease, an inborn error of copper metabolism with defect in hepatocellular copper transport, may cause both increased hepatic accumulation of copper and aggravation of the underlying hepatocellular degeneration.

For patients with cholestasis, biliary dysfunction, or cirrhosis, monitor hepatic and biliary function during long-term administration of Tralement. If a patient develops signs or symptoms of hepatic or biliary dysfunction during the use of Tralement, obtain serum concentrations of copper and ceruloplasmin as well as manganese whole blood concentrations. Consider using individual trace element products in patients with hepatic and/or biliary dysfunction [see Use in Specific Populations (8.6)].

5.5 Aluminum Toxicity

Tralement contains aluminum that may be toxic. Aluminum may reach toxic levels with prolonged parenteral administration if kidney function is impaired. Preterm infants, including preterm neonates, are particularly at risk because their kidneys are immature and they require large amounts of calcium and phosphate solutions, which contain aluminum.

Research indicates that patients with impaired kidney function, including preterm infants and premature neonates, who receive parenteral levels of aluminum at greater than 4 to 5 mcg/kg/day accumulate aluminum at levels associated with central nervous system and bone toxicity. Tissue loading may occur at even lower rates of administration or lower daily amounts.

Exposure to aluminum from Tralement is no more than 0.1 mcg/kg/day. When prescribing Tralement for use in parenteral nutrition containing other small volume parenteral products, the total daily patient exposure to aluminum from the admixture should be considered and maintained at no more than 5 mcg/kg/day [see Use in Specific Populations (8.4)].

5.6 Monitoring and Laboratory Tests

Monitor blood zinc, copper, manganese, and selenium concentrations, fluid and electrolyte status, serum osmolarity, blood glucose, liver and kidney function, blood count, and coagulation parameters during use of parenteral nutrition containing Tralement [see Dosage and Administration (2.4)].

5.7 Hypersensitivity Reactions with Zinc and Copper

Hypersensitivity reactions to subcutaneously administered zinc-containing insulin products and copper-containing intrauterine devices (IUD) were identified in postmarketing case reports. If hypersensitivity reactions occur in patients receiving Tralement in parenteral nutrition, discontinue Tralement, and initiate appropriate medical treatment [see Contraindications (4)].

Zinc
For patients prescribed zinc-containing insulin products, reported reactions included injection site induration, erythema, pruritus, papular rash, generalized urticaria, facial swelling, and dyspnea. Patients did not manifest symptoms after changing to zinc-free insulin or another insulin product with a reduced amount of zinc. In some cases, allergy testing confirmed the allergy to the zinc component of the insulin product.

Copper
For women with copper IUD implantation, reported reactions included diffuse eczematous dermatitis, maculopapular skin eruption, urticaria, and angioedema of the eyelids, face, and labia weeks or months after IUD insertion. In most cases, the patch test for copper was positive, and the adverse reactions resolved after IUD removal.

6 ADVERSE REACTIONS

The following adverse reactions were identified in clinical studies or post-marketing reports. Given that some of these reactions were reported voluntarily from a population of uncertain size, it is not always possible to reliably estimate their frequency or establish a causal relationship to drug exposure.

Adverse reactions with other components of parenteral nutrition solutions:
• Pulmonary embolism due to pulmonary vascular precipitates [see Warnings and Precautions (5.1)]
• Vein damage and thrombosis [see Warnings and Precautions (5.2)]
• Aluminum toxicity [see Warnings and Precautions (5.5)]
Adverse reactions with the use of trace elements administered parenterally or by other routes of administration:
• Neurologic toxicity with manganese [see Warnings and Precautions (5.3)]
• Hepatic accumulation of copper and manganese [see Warnings and Precautions (5.4)]
• Hypersensitivity reactions with zinc and copper [see Warnings and Precautions (5.7)]

8 USE IN SPECIFIC POPULATIONS

8.1 Pregnancy

Risk Summary
Administration of the recommended dose of Tralement in parenteral nutrition is not expected to cause major birth defects, miscarriage, or adverse maternal or fetal outcomes. Deficiency of trace elements may result in adverse pregnancy and fetal outcomes (see Clinical Considerations). Animal reproduction studies have not been conducted with Tralement or with the individual trace elements.

The estimated background risk of major birth defects and miscarriage for the indicated populations is unknown. All pregnancies have a background risk of birth defect, loss, or other adverse outcomes. In the U.S. general population, the estimated background risk of major birth defects and miscarriage in clinically recognized pregnancies is 2 to 4% and 15 to 20%, respectively.

Clinical Considerations
Disease-associated Maternal and/or Embryo-Fetal Risk
Deficiencies of trace elements, including zinc, copper, manganese, and selenium are associated with adverse pregnancy and fetal outcomes. Pregnant women have an increased metabolic demand for trace elements. Parenteral nutrition with Tralement should be considered if a pregnant woman’s nutritional requirements cannot be fulfilled by oral or enteral intake.

8.2 Lactation

Risk Summary

Zinc, copper, manganese, and selenium are present in human milk. Administration of the approved recommended dose of Tralement in parenteral nutrition is not expected to cause harm to a breastfed infant. There is no information on the effects of zinc sulfate, cupric sulfate, manganese sulfate, or selenious acid on milk production. The developmental and health benefits of breastfeeding should be considered, along with the mother’s clinical need for Tralement and any potential adverse effects on the breastfed infant from Tralement or from the underlying maternal condition.

8.4 Pediatric Use

Tralement is approved for use in pediatric patients weighing at least 10 kg as a source of zinc, copper, manganese, and selenium for parenteral nutrition when oral or enteral nutrition is not possible, insufficient, or contraindicated. Safety and dosing recommendations in pediatric patients are based on published literature describing controlled studies of products containing zinc, copper, manganese, and selenium [see Dosage and Administration (2.2)].

Tralement is not approved for use in pediatric patients weighing less than 10 kg because the product does not provide an adequate dosage of zinc, copper, or selenium to meet the needs of this subpopulation and exceeds the recommended dosage of manganese.

8.5 Geriatric Use

Reported clinical experience has not identified a difference in requirements for zinc, copper, manganese, or selenium between elderly and younger patients.

8.6 Hepatic Impairment

Copper is primarily excreted in the bile. Excretion is decreased in patients with cholestasis and/or cirrhosis. Manganese is found, and presumed to be excreted, in bile [see Clinical Pharmacology (12.3)]. Hepatic accumulation of copper and manganese have been reported with long-term administration in parenteral nutrition at dosages higher than recommended [see Warnings and Precautions (5.4)].

For patients with cholestasis, biliary dysfunction, or cirrhosis, monitor hepatic and biliary function during long-term administration of Tralement. If a patient develops signs or symptoms of hepatic or biliary dysfunction during use of Tralement, obtain serum concentrations of copper and ceruloplasmin as well as manganese whole blood concentrations. Consider using individual trace element products in patients with hepatic and/or biliary dysfunction.

10 OVERDOSAGE

There is no information on overdos Management of overdosage is supportive care based on presenting signs and symptoms. Obtain blood
samples for laboratory testing of the individual trace elements and ceruloplasmin for copper.

Zinc
Acute zinc toxicity was reported in an infant who received an inadvertent 1,000-fold overdose of zinc in parenteral nutrition that led to cardiac failure and death. Zinc toxicity in adult patients receiving 17 to 400-fold the recommended dosage in parenteral nutrition for 2.5 to 60 days reported signs and
symptoms including vomiting, diarrhea, hyperamylasemia, thrombocytopenia, and anemia. The zinc serum concentration was 2 to 30-fold the upper end of the reported range in healthy subjects in these cases.

Copper
Acute copper toxicity was reported in patients with oral, intravenous, or subcutaneous administration. Clinical manifestations included metallic taste, nausea, vomiting, abdominal pain, and multi-organ failure involving kidney, liver, blood, and cardiovascular systems. Chelating agents can be used for treatment of acute toxicity. Long-term administration of parenteral copper above recommended dosage may result in significant accumulation of copper in the liver, brain, and other tissues with possible organ damage [see Warnings and Precautions (5.4)].
Manganese
Acute manganese toxicity was reported in adult patients following infusion of manganese more than 10,000-fold the recommended dosage and after use of dialysis fluid contaminated with manganese. Signs and symptoms included skin flushing, acute pancreatitis, elevated whole blood manganese concentrations, and MRI evidence of brain accumulation of manganese. Chronic infusion and oral intake of manganese above recommended dosage have resulted in neuropsychiatric symptoms and MRI evidence of brain accumulation of manganese [see Warnings and Precautions (5.3)].

Selenium
Acute selenium toxicity was reported with oral overdosage of greater than 1 g/day. Symptoms included nausea, vomiting, diarrhea, abdominal pain, garlic breath odor, and altered mental status. Death from circulatory collapse was reported after oral ingestion of 5 to 10 g of selenium with blood concentrations ranging 10 to 50-fold the upper end of the reported range in healthy subjects.

11 DESCRIPTION

Tralement® (trace elements injection 4*, USP) is a sterile, non-pyrogenic, clear, and colorless to slightly blue solution, intended for use as a combination of four trace elements and an additive to intravenous solutions for parenteral nutrition. It contains no preservative.

Each single-dose vial contains 1 mL and each multiple-dose vial contains 10 mL. *Each mL contains zinc 3 mg (equivalent to zinc sulfate 7.41 mg), copper 0.3 mg (equivalent to cupric sulfate 0.75 mg), manganese 55 mcg (equivalent to manganese sulfate 151 mcg), selenium 60 mcg (equivalent to selenious acid 98 mcg), and water for injection. Sulfuric acid may be added to adjust pH between 1.5 and 3.5.

Zinc sulfate exists as a heptahydrate. The structural formula is:

Molecular formula: ZnSO4 • 7H2O.
Molecular weight: 287.54 g/mol.

Cupric sulfate exists as a pentahydrate. The structural formula is:

Molecular formula: CuSO4 • 5H2O.
Molecular weight: 249.69 g/mol.

Manganese sulfate exists as a monohydrate. The structural formula is:

Molecular formula: MnSO4 • H2O.

Molecular weight: 169.02 g/mol.

The structural formula of selenious acid is:

Molecular formula: H2SeO3.
Molecular weight: 128.97 g/mol.

Tralement contains no more than 6,000 mcg/L of aluminum.

12 CLINICAL PHARMACOLOGY

12.1 Mechanism of Action

Zinc
Zinc functions as a cofactor of various enzymes including DNA polymerases, RNA polymerases, alcohol dehydrogenase, and alkaline phosphatases. Zinc is a coordinator of protein structural folding that interacts with a variety of proteins, lipids, and nucleic acids. In addition, zinc is a catalyst of essential biochemical reactions, including activation of substrates of carbonic anhydrase in erythrocyte.
Copper
Copper is a cofactor for many metalloenzymes acting as an oxidase to achieve reduction of molecular oxygen. Examples of copper metalloenzymes include but are not limited to lysyl oxidase, monoamine oxidase, ferroxidase, cytochrome C oxidase, dopamine beta monooxygenase, tyrosinase, and superoxide dismutase.\

Manganese
Manganese is essential for the normal catalytic activity of several metalloenzymes including manganese superoxide dismutase, arginase, glutamine synthetase, phosphoenolpyruvate decarboxylase, and pyruvate carboxylase. Manganese contributes to the normal function of several other enzyme families
including the oxidoreductases, transferases, hydrolases, lyases, isomerases, and ligases.

Selenium
Selenious acid is converted in vivo to hydrogen selenide via glutathione-involved electron reductions. Hydrogen selenide acts as a selenium pool to form selenoproteins which include, but are not limited to, glutathione peroxidase, iodothyronine deiodinase, peroxidase, and thioredoxins.

12.2 Pharmacodynamics

The exposure-response relationship and the time course of pharmacodynamic response are unknown for zinc, copper, manganese, and selenium.

12.3 Pharmacokinetics

Zinc
Over 85% of total body zinc is found in skeletal muscle and bone. In blood, zinc is mainly localized within erythrocytes. Approximately 80% of serum zinc is bound to albumin and the remainder to α-2-macroglobulin and amino acids. In adults, zinc is primarily excreted via the gastrointestinal tract and eliminated in the feces. A smaller amount of zinc is excreted via the kidneys in the urine. Urinary zinc excretion rates in very low birth weight preterm infants are relatively high in the neonatal period, and they decline to a level on a body weight basis that is similar to that of normal adults by two months of age.
Copper
In plasma, about 7% of copper is bound to albumin and amino acids. In the liver, about 93% of copper is bound to ceruloplasmin and released to the serum. Copper is excreted in bile and into the gastrointestinal tract where it is not reabsorbed. Copper is also eliminated through the kidneys.
Manganese
Manganese is widely distributed in body tissues including liver and specific brain regions such as the basal ganglia. The concentrations of manganese are higher in erythrocytes compared to the plasma or serum concentrations. In human plasma, manganese is bound to albumin and β1-globulin. Manganese is
found in human bile suggesting biliary excretion.

Selenium
In humans, 85% of intravenous administered 75Se was protein-bound within 4 to 6 hours and 95% by 24 hours.

16 HOW SUPPLIED

Tralement (trace elements injection 4*, USP) is a clear, colorless to slightly blue solution supplied as follows:

NDC 0517-9305-01 1 mL single-dose vial

NDC 0517-9305-25 Packaged in trays containing 25 vials per tray

*Each mL of Tralement contains zinc 3 mg, copper 0.3 mg, manganese 55 mcg, and selenium 60 mcg.

Vial closure is not made with natural rubber latex.

Store at 20°C to 25°C (68°F to 77°F); excursions permitted to 15°C to 30°C (59°F to 86°F) [See USP Controlled Room Temperature].

Store admixed solution at 2ºC to 8ºC (36ºF to 46ºF) [see Dosage and Administration (2.3)].

17 PATIENT COUNSELING INFORMATION

Inform patients, caregivers, and home healthcare providers of the following risks of Tralement:

• Pulmonary embolism due to pulmonary vascular precipitates [see Warnings and Precautions (5.1)]
• Vein damage and thrombosis [see Warnings and Precautions (5.2)]
• Neurologic toxicity with manganese [see Warnings and Precautions (5.3)]
• Hepatic accumulation of copper and manganese [see Warnings and Precautions (5.4)]
• Aluminum toxicity [see Warnings and Precautions (5.5)]
• Hypersensitivity reactions with zinc and copper [see Warnings and Precautions (5.7)

Distributed by:

IN9305

PRINCIPAL DISPLAY PANEL - Container Label (1 mL)

0517-9305-01
Rx Only
Tralement® (trace elements injection 4*, USP)
*Each mL provides: zinc 3 mg, copper 0.3 mg, manganese 55 mcg, and selenium 60 mcg

Contains no more than 6,000 mcg/L of aluminum.
For intravenous infusion after admixing

For use in adult and pediatric patients weighing at least 10 kg
1 mL Single-Dose Vial
Discard Unused Portion

PRINCIPAL DISPLAY PANEL - Carton Labeling (1 mL)

0517-9305-25
Rx Only
Tralement® (trace elements injection 4*, USP)
*Each mL provides: zinc 3 mg, copper 0.3 mg, manganese 55 mcg, and selenium 60 mcg

For intravenous infusion after admixing

For use in adult and pediatric patients weighing at least 10 kg
25 x 1 mL Single-Dose Vials
Discard Unused Portion